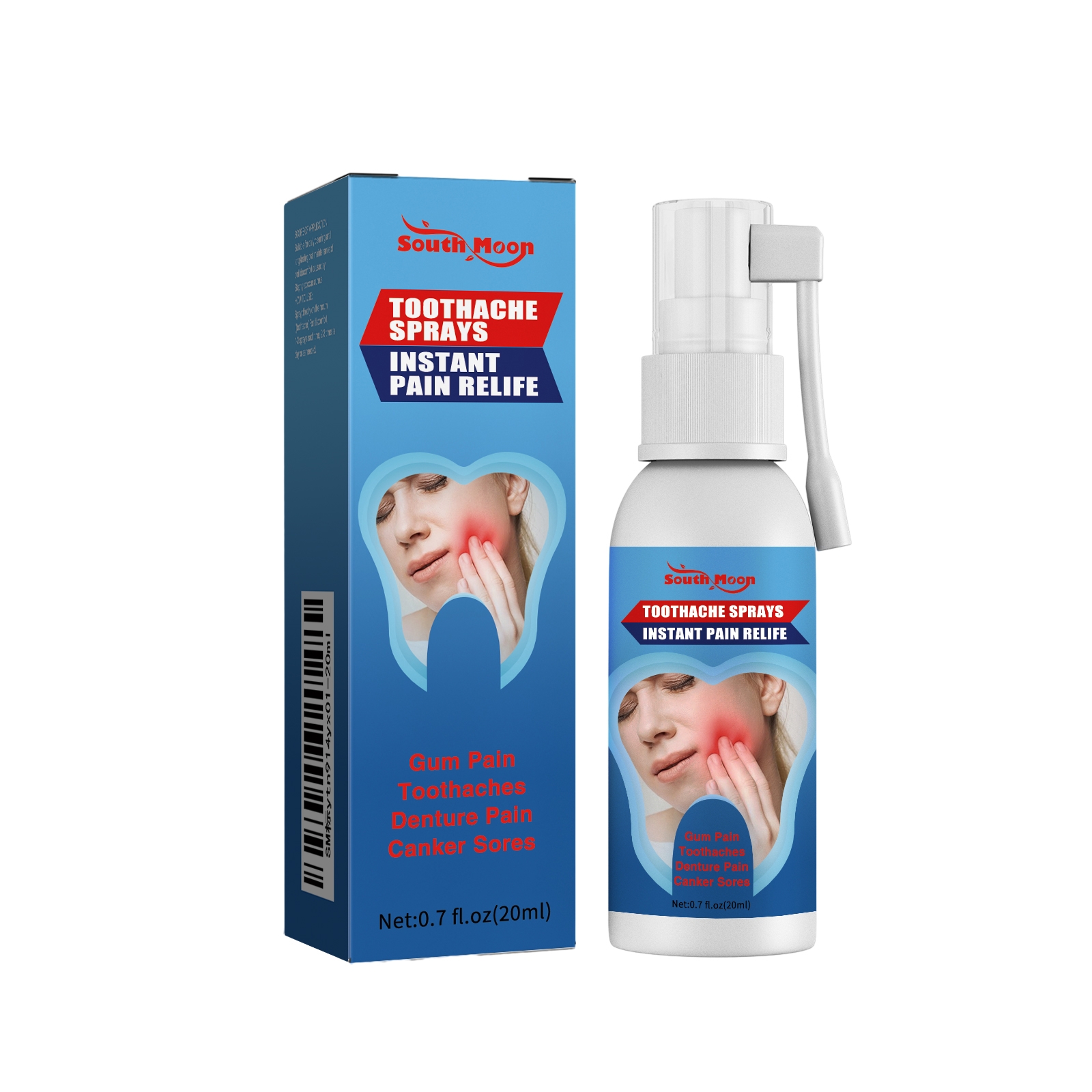 DRUG LABEL: SOUTH MOON Toothache
NDC: 84983-005 | Form: LIQUID
Manufacturer: Shantou South Moon Biotechnology Co., Ltd.
Category: otc | Type: HUMAN OTC DRUG LABEL
Date: 20251127

ACTIVE INGREDIENTS: MENTHA X PIPERITA WHOLE 0.06 mg/20 mg
INACTIVE INGREDIENTS: AQUA 19.286 mg/20 mg; GLYCERIN 0.6 mg/20 mg; 1,2-HEXANEDIOL 0.02 mg/20 mg; THIAMINE 0.01 mg/20 mg; GLUCONOLACTONE 0.02 mg/20 mg; ALLANTOIN 0.004 mg/20 mg

ACTIVE INGREDIENT

MENTHA X PIPERITA WHOLE

WHEN USING

Spray directly on the mouth (toothache) For discomfort, 1-3 sprays each time, 2-3 times a day or as needed.

PURPOSE

Suitable for daily cleaning and long-lasting oral maintenance of oral discomfort caused by Staphylococcus aureus.

DO NOT USE

Discontinue use if signs of irritation or rash occur.

STOP USE

Discontinue use if signs of irritation or rash occur.

KEEP OUT OF REACH OF CHILDREN

Please keep out of reach of children. Do not swallow.

WARNINGS

Please keep out of reach of children. Do not swallow.Please clean your hands before use to ensure the best results from the product. Discontinue use if signs of irritation or rash occur. Store in a cool and dry place.

STORAGE AND HANDLING

Store in a cool and dry place.

INACTIVE INGREDIENT

AQUA、GLYCERIN、GLUCONOLACTONE、1,2-HEXANEDIOL、VITAMIN B1、ALLANTOIN